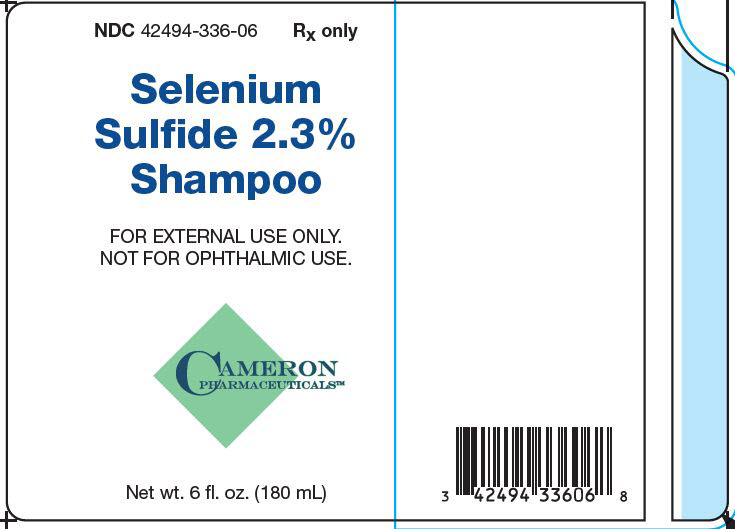 DRUG LABEL: Selenium Sulfide
NDC: 42494-336 | Form: SHAMPOO
Manufacturer: Cameron Pharmaceuticals, LLC
Category: prescription | Type: HUMAN PRESCRIPTION DRUG LABEL
Date: 20210401

ACTIVE INGREDIENTS: SELENIUM SULFIDE 23 mg/1 mL
INACTIVE INGREDIENTS: AMMONIUM LAURYL SULFATE; TRICAPRIN; CHROMIC OXIDE; CITRIC ACID MONOHYDRATE; COCAMIDOPROPYL BETAINE; FLUORESCEIN SODIUM; DIAZOLIDINYL UREA; DISTEARYL PHTHALAMIC ACID; EDETATE DISODIUM; HYPROMELLOSE, UNSPECIFIED; MAGNESIUM ALUMINUM SILICATE; METHYLPARABEN; PANTHENOL; PPG-2 HYDROXYETHYL COCO/ISOSTEARAMIDE; PROPYLENE GLYCOL; PROPYLPARABEN; WATER; FD&C RED NO. 40; SODIUM CITRATE, UNSPECIFIED FORM; TITANIUM DIOXIDE; .ALPHA.-TOCOPHEROL ACETATE; UREA; PYRITHIONE ZINC

Selenium Sulfide
2.3% Shampoo

DESCRIPTION:

Each mL contains 23 mg of selenium sulfide in a vehicle consisting of: ammonium lauryl sulfate, caprylic/capric triglyceride, chromium oxide green, citric acid, cocamidopropyl betaine, D&C yellow no 8, diazolidinyl urea, distearyl phthalic acid amide, edetate disodium, fragrance, hydroxypropyl methylcellulose, magnesium aluminum silicate, methylparaben, panthenol, PPG-2 hydroxyethyl coco/isostearamide, propylene glycol, propylparaben, purified water, FD&C red no 40, sodium citrate, titanium dioxide, tocopheryl acetate, urea, and zinc pyrithione.

CLINICAL PHARMACOLOGY:

Selenium sulfide appears to have a cytostatic effect on cells of the epidermis and follicular epithelium, reducing corneocyte production.

Pharmacokinetics:

The mechanism of action of topically applied selenium sulfide is not yet known.

INDICATIONS:

Selenium Sulfide 2.3% Shampoo is a liquid antiseborrheic, antifungal preparation useful for the treatment of seborrheic dermatitis of the scalp, dandruff and tinea versicolor. Urea hydrates and is useful for conditions such as dry scalp.

CONTRAINDICATIONS:

Selenium Sulfide 2.3% Shampoo is contraindicated in persons with known or suspected hypersensitivity to any of the ingredients of the product.

WARNINGS:

PRECAUTIONS: FOR EXTERNAL USE ONLY. NOT FOR OPHTHALMIC USE.

Avoid contact with eyes, lips and mucous membranes.

General:

Selenium Sulfide 2.3% Shampoo is to be used as directed by a licensed medical practitioner and should not be used to treat any condition other than that for which it was prescribed. If redness or irritation occurs, discontinue use and consult a licensed medical practitioner.

Information for Patients:

Patients should discontinue the use of Selenium Sulfide 2.3% Shampoo if the condition becomes worse or if a rash develops in the area being treated or elsewhere. Avoid contact with eyes, lips and mucous membranes.

Carcinogenesis, Mutagenesis and Impairment of Fertility:

Dermal application of 25% and 50% solutions of 2.5% selenium sulfide lotion on mice over an 88-week period indicated no carcinogenic effects. Studies on reproduction and fertility also have not been performed.

Pregnancy: Category C.

Animal reproduction studies have not been conducted with this product. It is also not known whether this product can affect reproduction capacity or cause fetal harm when administered to a pregnant woman. This product should be used by a pregnant woman only if clearly needed or when potential benefits outweigh potential hazards to the fetus.

Nursing Mothers:

It is not known whether this drug is excreted in human milk. Because many drugs are excreted in human milk, caution should be exercised when this product is administered to a nursing woman.

Pediatric use:

Safety and effectiveness in children under the age of 12 years have not been established.

ADVERSE REACTIONS:

In decreasing order of severity: skin irritation; occasional reports of increase in normal hair loss; discoloration of hair (can be avoided or minimized by thorough rinsing of hair after treatment). As with other shampoos, oiliness or dryness of hair and scalp may occur.

Call your licensed medical practitioner for medical advice about side effects. To report a serious adverse event, call 1-888-767-7913.

OVERDOSAGE:

There are no documented reports of serious toxicity in humans resulting from acute ingestion of this product. However, acute toxicity studies in animals suggest that ingestion of large amounts could result in potential human toxicity. Evacuation of the stomach contents should be considered in cases of acute oral ingestion.

DOSAGE AND ADMINISTRATION:

For seborrheic dermatitis and dandruff: Wet skin and apply to areas to be cleansed. Massage gently into the skin working into a full lather. Rinse thoroughly and pat dry. Generally, two applications each week for two weeks will control symptoms. Subsequently, shampoo may be used less frequently, or as directed by a licensed medical practitioner. It should not be applied more frequently than necessary to maintain control.

For tinea versicolor: Wet skin and apply to areas to be cleansed. Massage gently into the skin working into a full lather. Allow product to remain on skin for ten minutes, then rinse thoroughly and pat dry. Repeat procedure once a day for seven days, or as directed by a licensed medical practitioner.

HOW SUPPLIED:

Selenium Sulfide 2.3% Shampoo is supplied in a 6 fl. oz. (180 mL) bottle, NDC 42494-336-06.

STORAGE:

Store at 20-25°C (68-77°F); excursions permitted between 15° and 30°C (59° and 86°F). See USP Controlled Room Temperature.

Protect from freezing and excessive heat. Keep bottle tightly closed.

All prescriptions using this product shall be pursuant to state statutes as applicable. This is not an Orange Book product. This product has not been evaluated for therapeutic equivalence.

KEEP OUT OF REACH OF CHILDREN

Rx only

Manufactured for:

Cameron Pharmaceuticals, LLC 1009 Twilight Trail

Frankfort, Kentucky 40601

Rev. 08/2015

Principal Display Panel - 180 mL Bottle Carton

NDC 42494-336-06

Selenium Sulfide 2.3% Shampoo

FOR EXTERNAL USE ONLY. NOT FOR OPHTHALMIC USE

Cameron Pharmaceuticals™

Net wt. 6 fl. oz. (180 mL)